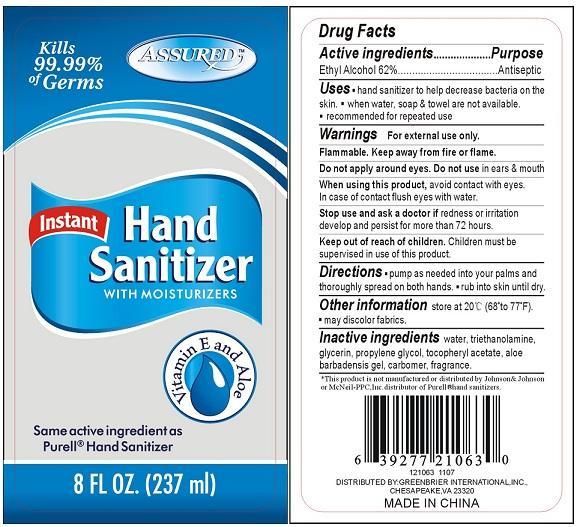 DRUG LABEL: Assured Instant Hand Sanitizer with Moisturizers Vitamin E and Aloe
NDC: 33992-1063 | Form: GEL
Manufacturer: Greenbrier International, Inc.
Category: otc | Type: HUMAN OTC DRUG LABEL
Date: 20150218

ACTIVE INGREDIENTS: ALCOHOL 62 mL/100 mL
INACTIVE INGREDIENTS: WATER; TROLAMINE; GLYCERIN; PROPYLENE GLYCOL; ACETATE ION; ALOE VERA LEAF; CARBOMER HOMOPOLYMER TYPE C

Assured Instant Hand Sanitizer With Moisturizers Vitamin E and Aloe

Active Ingredient

Ethyl Alcohol 62%

Purpose

Antiseptic

Uses

Hand sanitizer to help decrease bacteria on the skin.
When water, soap and towel are not available.
Recommended for repeated use.

Warnings

For external use only.

Flammable. Keep away from fire or flame.

Do not apply around eyes. Do not use in ears and mouth.

When using this product,

avoid contact with eyes.

In case of contact flush eyes with water.

Stop use and ask a doctor if

redness or irritation develop and persist for more than 72 hours.

Keep out of reach of children

Children must be supervised in use of this product.

Directions

Pump as needed into your palms and thoroughly spread on both hands.

Rub into skin until dry.

Other Information

Store at 120 degrees C 68 degrees to 77 degrees F

May discolor fabrics.

Inactive Ingredients

water, triethanolamine , glycerin, propylene glycol, tocopheryl acetate, aloe barbadensis gel carbomer, fragrance.

This product is not manufactured or distributed by Johnson and Johnson

or McNeil-PPC, Inc. distributor of Purell hand sanitizers.

Distributed By: GREENBRIAR INTERNATIONAL, INC.,

CHESAPEAKE, VA 23320

MADE IN CHINA

PACKAGE LABEL

ASSURED

Kills 99.99 percent of Germs

Instant Hand Sanitizer

with Moisturizers

Vitamin E and Aloe

Same active ingredient as Purell Hand Sanitizer

8 FL OZ. 237 ml